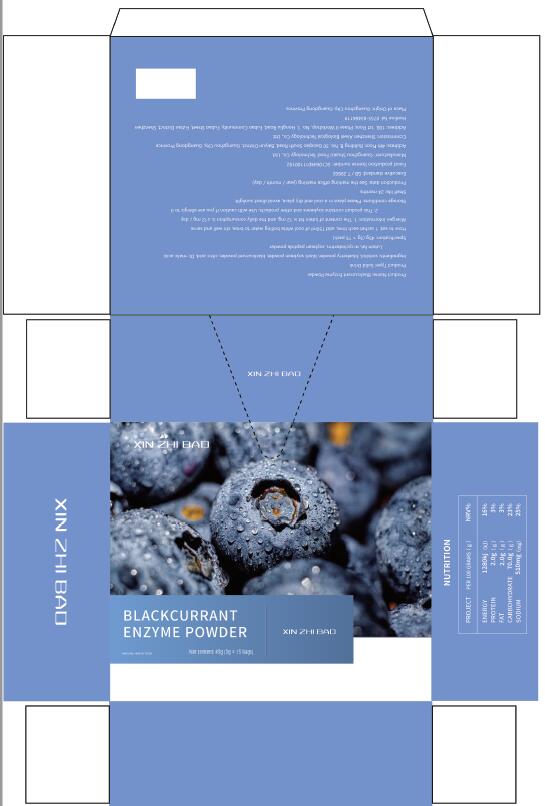 DRUG LABEL: BlackcurrantEnzymePowder
NDC: 55030-003 | Form: POWDER
Manufacturer: Shenzhen Aiwei Biological Technology Co., Ltd.
Category: homeopathic | Type: HUMAN OTC DRUG LABEL
Date: 20200611

ACTIVE INGREDIENTS: .BETA.-CAROTENE 0.36 g/3 g; KERACYANIN 0.45 g/3 g; LUTEIN 0.6 g/3 g; .BETA.-CAROTENE, (9Z)- 0.45 g/3 g; STRAWBERRY 0.3 g/3 g; MALTODEXTRIN 0.3 g/3 g; CRANBERRY 0.36 g/3 g
INACTIVE INGREDIENTS: SILICON DIOXIDE; ASCORBIC ACID; CITRIC ACID MONOHYDRATE

DOSAGE AND ADMINISTRATION

4g/bag, 1 bag a day

WARNINGS

Please keep out of the reach of children

INACTIVE INGREDIENT

Citric acid , sucralose , silica

INDICATIONS AND USAGE

: 2 times a day, 1-2 sachets each time, open the bag to eat or take it with warm water, or add it to juice and drinks

keep out of reach of children

PURPOSE

Replenish the protein needed by the body

ACTIVE INGREDIENT

sorbitol, blueberry powder, black soybean powder, blackcurrant powder, citric acid, DL malic acid,
Lutein fat, a-cyclodextrin, soybean peptide powder